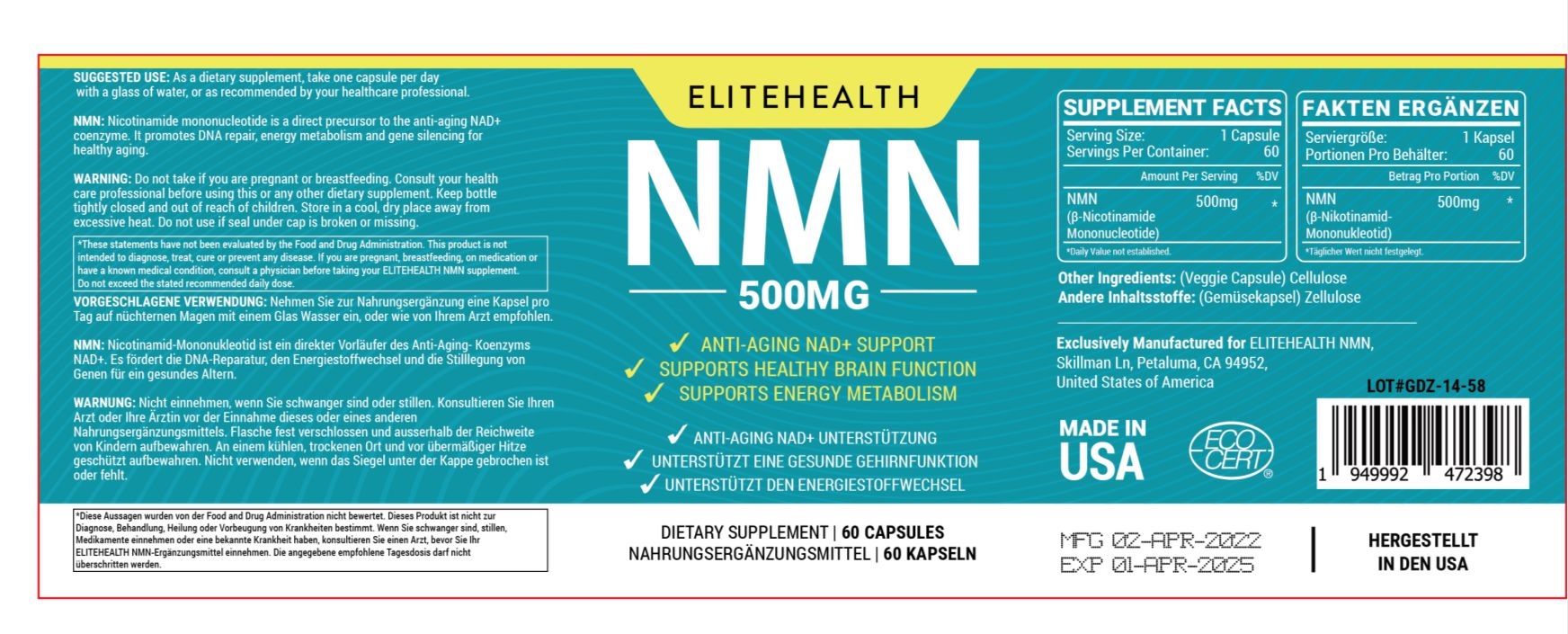 DRUG LABEL: ELITEHEALTH
NDC: 83458-003 | Form: CAPSULE
Manufacturer: MOHAMMEDJALI Co., Ltd
Category: otc | Type: HUMAN OTC DRUG LABEL
Date: 20230526

ACTIVE INGREDIENTS: NICOTINAMIDE MONONUCLEOTIDE 500 mg/1 1
INACTIVE INGREDIENTS: POWDERED CELLULOSE

Active ingredient

β-Nicotinamide Mononucleotide 500mg

Warning

Do not take if you are pregnant or breastfeeding. Consult your health care professional before using this or any other dietary supplement. Keep bottle tightly closed and out of reach of children.

Direction

As a dietary supplement, take one capsule per day with a glass of water, or as recommended by your healthcare professional.

Inactive ingredient

Cellulose (Veggie Capsule)

Other information

Store in a cool, dry place away from excessive heat. Do not use if seal under cap is broken or missing.